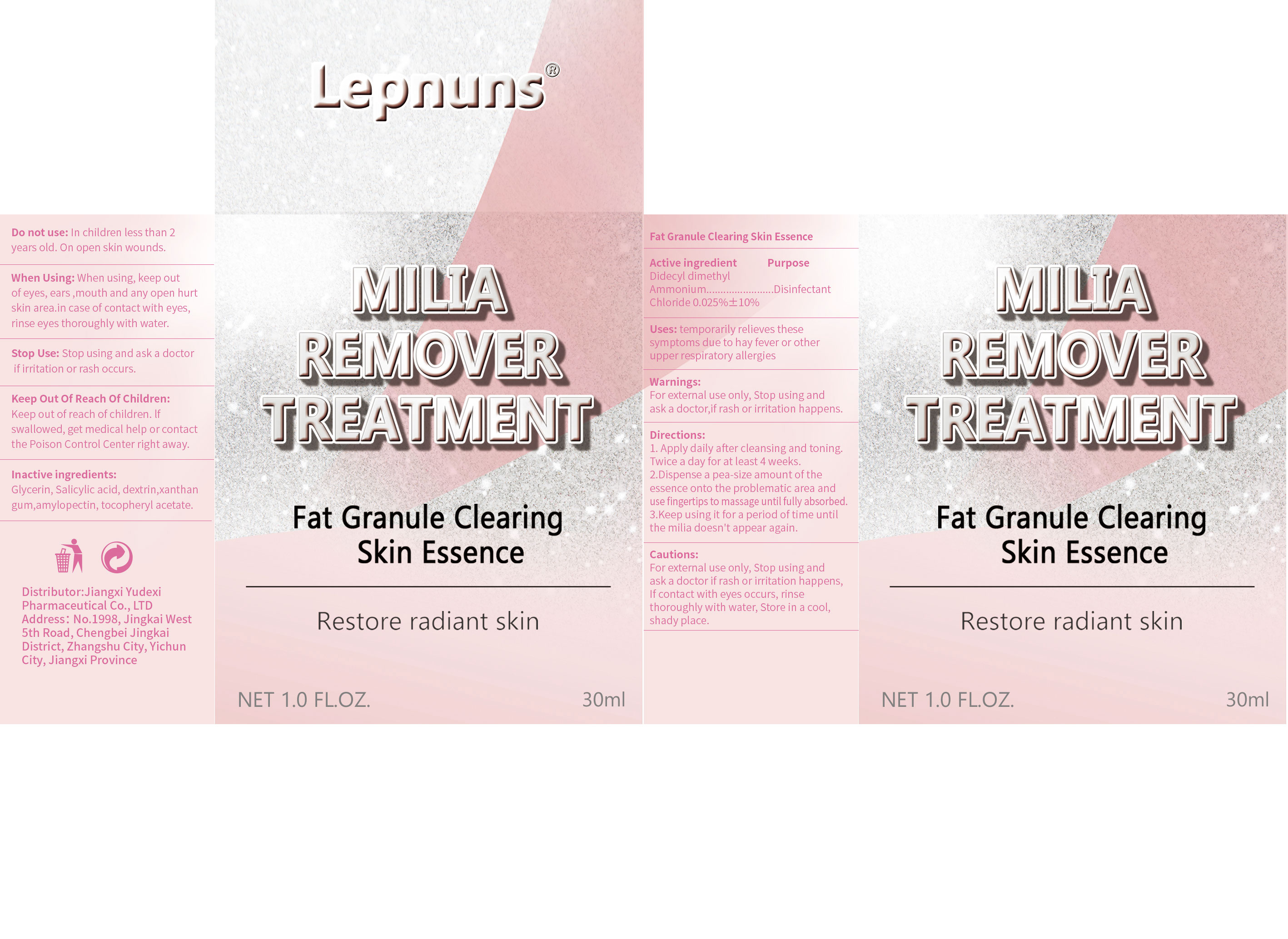 DRUG LABEL: Lepnuns  MILIA REMOVER
NDC: 85248-020 | Form: LIQUID
Manufacturer: Jiangxi Yudexi Pharmaceutical Co., LTD
Category: otc | Type: HUMAN OTC DRUG LABEL
Date: 20260128

ACTIVE INGREDIENTS: DIDECYLDIMONIUM CHLORIDE 0.25 g/100 mL
INACTIVE INGREDIENTS: GLYCERIN; DEXTRIN, CORN; XANTHAN GUM; .ALPHA.-TOCOPHEROL ACETATE; AMYLOPECTIN, CORN; SALICYLIC ACID

85248-020

Active Ingredient

Didecyl dimethyl Ammonium Chloride 0.025%士10%

Purpose

Disinfectant

Use

temporarily relieves these symptoms due to hay fever or other upper respiratory allergies.

Warnings

For external use only, Stop using and ask a doctor,if rash or irritation happens.

Do not use

In children less than 2 years old. On open skin wounds.

When Using

When using, keep out of eyes, ears ,mouth and any open hurt skin area.in case of contact with eyes, rinse eyes thoroughly with water.

Stop Use

Stop using and ask a doctor if ir irritation or rash occurs.

Ask Doctor

Stop using and ask a doctor if ir irritation or rash occurs.

Keep Oot Of Reach Of Children

Keep out of reach of children. lf swallowed, get medical help or contact the Poison Control Center right away.

Directions

1. Apply daily after cleansing and toning.Twice a day for at least 4 weeks. 2.Dispense a pea-size amount of the essence onto the problematic area and use fingertips to massage until fully absorbed. 3,Keep using it for a period of time until the milia doesn't appear again.

Other information

For external use only, Stop using and ask a doctor if rash or irritation happens， lf contact with eyes occurs. rinse thoroughly with water, Store in a cool,shady place.

Inactive ingredients

Glycerin, Salicylic acid, dextrin,xanthan gum,amylopectin, tocopheryl acetate.